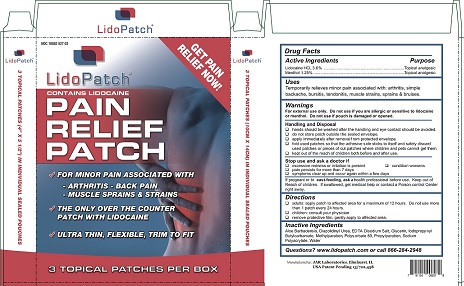 DRUG LABEL: Lidopatch
NDC: 70267-001 | Form: PATCH
Manufacturer: Wuhan Bingbing Pharmaceutical Co., Ltd
Category: otc | Type: HUMAN OTC DRUG LABEL
Date: 20190128

ACTIVE INGREDIENTS: LIDOCAINE 0.036 mg/1 1; MENTHOL 0.0125 mg/1 1
INACTIVE INGREDIENTS: COBALT DISODIUM EDETATE; GLYCERIN; IODOPROPYNYL BUTYLCARBAMATE; POLYSORBATE 80; PROPYLPARABEN; SODIUM POLYACRYLATE (2500000 MW); WATER; DIAZOLIDINYL UREA; ALOE VERA LEAF; METHYLPARABEN

Lidopatch

WARNINGS SECTION
For external use only. Do not use if you are allergic or sensitive to lidocaine or menhol. Do not use if pouch is damaged or opened.

PURPOSE

Temporarily relieves minor pain associated with: arthritis, simple backache, bursitis, tendonitis, muscle straints, sprains and bruises.

ACTIVE INGREDIENT SECTION
Lidocaine HCL 3.6% - Topical analgesic
Menthol 1.25% - Topical analgesic

STOP USE SECTION
Stop Use and ask doctor if:
excessive redness or irritation is present
Pain persists for more than 7 days
symptoms cear up and occur again within a few days
conditions worsens
If pregnant or breasfeading, ask a health professional before use. keep out of reach of children. If swallowed, get medical help or contact a poison control center right away.

DOSAGE & ADMINISTRATION SECTION

Directions: Aduts apply patch to affected area for a maximum of 12 hours.
Do not use more than 1 patch every 24 hours.
children : consult your physician
remove protective film, gently apply to affected area.

INACTIVE INGREDIENT SECTION

Aloe Barbadensis, Diazolidinyl Urea, EDTA Disodium Salt, Glycerin, Iodpropynyl, Butylcarbonate, Methylparaben, Polysorbate 80, Propylparaben, Sodium Polyacrylate, Water

Usage
Aduts apply patch to affected area for a maximum of 12 hours.
Do not use more than 1 patch every 24 hours

KEEP OUT OF REACH OF CHILDREN.